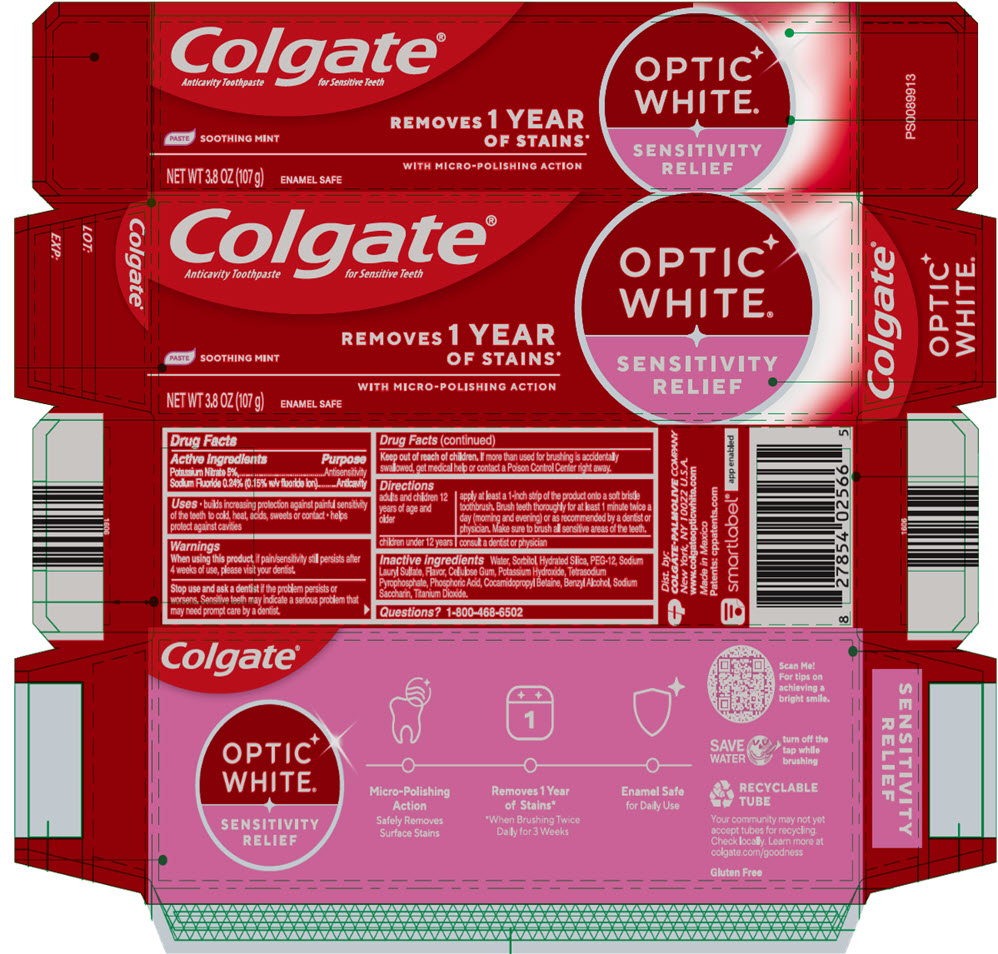 DRUG LABEL: COLGATE OPTIC WHITE RELIEF
NDC: 65954-834 | Form: PASTE, DENTIFRICE
Manufacturer: Mission Hills S.A de C.V
Category: otc | Type: HUMAN OTC DRUG LABEL
Date: 20251007

ACTIVE INGREDIENTS: SODIUM FLUORIDE 1.5 mg/1 g; POTASSIUM NITRATE 50 mg/1 g
INACTIVE INGREDIENTS: WATER 1777.69 mg/1 g; SORBITOL; HYDRATED SILICA; POLYETHYLENE GLYCOL 600; SODIUM LAURYL SULFATE; CARBOXYMETHYLCELLULOSE; POTASSIUM HYDROXIDE; SODIUM PYROPHOSPHATE; PHOSPHORIC ACID; COCAMIDOPROPYL BETAINE; BENZYL ALCOHOL; SACCHARIN SODIUM; TITANIUM DIOXIDE

COLGATE® OPTIC WHITE RELIEF

Drug Facts

ACTIVE INGREDIENT

Active ingredients | Purpose
Potassium Nitrate 5% | Antisensitivity
Sodium Fluoride 0.24% (0.15% w/v fluoride ion) | Anticavity

Uses

- builds increasing protection against painful sensitivity of the teeth to cold, heat, acids, sweets, or contact
- helps protect against cavities

Warnings

When using this product, if pain/sensitivity persists after 4 weeks, visit your dentist.

Stop use and ask a dentist if the problem persists or worsens. Sensitive teeth may indicate a serious problem that may need prompt care by a dentist.

Keep out of reach of children. If more than used for brushing is accidentally swallowed, get medical help or contact a Poison Control Center right away.

Directions

adults and children 12 years of age and older | apply at least a 1-inch strip of the product onto a soft bristle toothbrush. Brush teeth thoroughly for at least 1 minute twice a day (morning and evening) or as recommended by a dentist or physician. Make sure to brush all sensitive areas of the teeth.
children under 12 years | consult a dentist or physician

Inactive ingredients

Water, Sorbitol, Hydrated Silica, PEG-12, Sodium Lauryl Sulfate, Flavor, Cellulose Gum, Potassium Hydroxide, Tetrasodium Pyrophosphate, Phosphoric Acid, Cocamidopropyl Betaine, Benzyl Alcohol, Sodium Saccharin, Titanium Dioxide.

Questions?

1-800-468-6502

Dist. by:
COLGATE-PALMOLIVE COMPANY
New York, NY 10022 U.S.A.
www.colgateopticwhite.com

PRINCIPAL DISPLAY PANEL - 107 g Tube Carton

Colgate®
Anticavity Toothpaste for Sensitive Teeth

OPTIC
WHITE®
SENSITIVITY
RELIEF

PASTE SOOTHING MINT

REMOVES 1 YEAR
OF STAINS*
WITH MICRO-POLISHING ACTION

NET WT 3.8 OZ (107 g)

ENAMEL SAFE